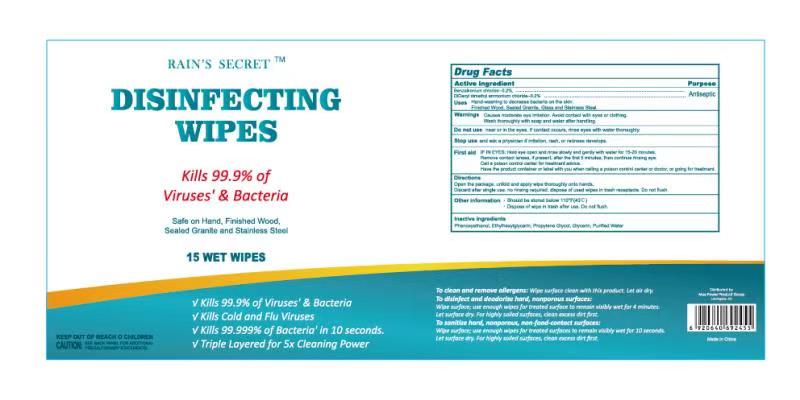 DRUG LABEL: DISINFECTING WIPES
NDC: 75328-501 | Form: CLOTH
Manufacturer: CROWN (YANGZHOU) HEALTH & BEAUTY CO., LTD.
Category: otc | Type: HUMAN OTC DRUG LABEL
Date: 20201112

ACTIVE INGREDIENTS: DIDECYLDIMONIUM CHLORIDE 0.2 1/100 1; BENZALKONIUM CHLORIDE 0.2 1/100 1
INACTIVE INGREDIENTS: ETHYLHEXYLGLYCERIN; PROPYLENE GLYCOL; GLYCERIN; PHENOXYETHANOL; WATER

DISINFECTING WIPES

DISINFECTING WIPES

Active Ingredient(s)

Benzalkonium Chloride 0.2%, w/w
DiDecyl dimethyl ammonium chloride 0.2%, w/w

Purpose

Antiseptic

Use

DISINFECTING WIPES to help reduce bacteria that potentially can cause disease. For use when soap and water are not available.

Warnings

For external use only. Flammable. Keep away from heat or flame

Do not use

- in children less than 2 months of age
- on open skin wounds

When using this product keep out of eyes, ears, and mouth. In case of contact with eyes, rinse eyes thoroughly with water.
Stop use and ask a doctor if irritation or rash occurs. These may be signs of a serious condition.
Keep out of reach of children. If swallowed, get medical help or contact a Poison Control Center right away.

Stop use and ask a doctor if irritation or rash occurs. These may be signs of a serious condition.

Keep out of reach of children. If swallowed, get medical help or contact a Poison Control Center right away.

Directions

- Place enough product on hands to cover all surfaces. Rub hands together until dry.
- Supervise children under 6 years of age when using this product to avoid swallowing.

Other information

- Store between 15-30C (59-86F)
- Avoid freezing and excessive heat above 40C (104F)

Inactive ingredients

Phenoxyethanol
Ethylhexyl glycerin
Propylene Glycol
Glycerin
Purified Water